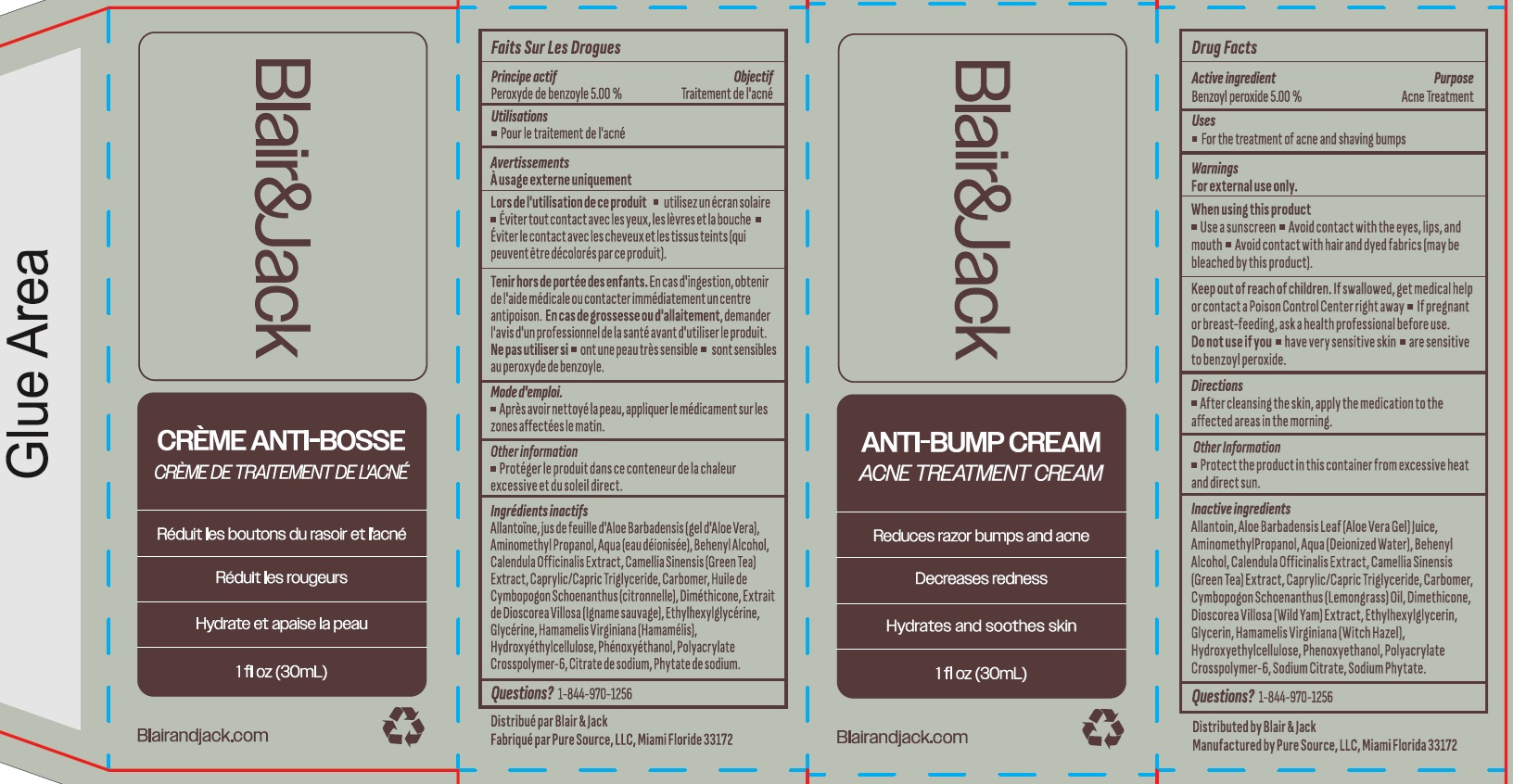 DRUG LABEL: BLAIR and JACK Anti-Bump Acne Treatment
NDC: 84377-489 | Form: CREAM
Manufacturer: Blair + Jack
Category: otc | Type: HUMAN OTC DRUG LABEL
Date: 20240611

ACTIVE INGREDIENTS: BENZOYL PEROXIDE 50 mg/1 mL
INACTIVE INGREDIENTS: ALLANTOIN; ALOE VERA LEAF; AMINOMETHYLPROPANOL; WATER; DOCOSANOL; CALENDULA OFFICINALIS FLOWER; GREEN TEA LEAF; MEDIUM-CHAIN TRIGLYCERIDES; CARBOMER HOMOPOLYMER, UNSPECIFIED TYPE; CYMBOPOGON SCHOENANTHUS OIL; DIMETHICONE; DIOSCOREA VILLOSA TUBER; ETHYLHEXYLGLYCERIN; GLYCERIN; HAMAMELIS VIRGINIANA ROOT BARK/STEM BARK; HYDROXYETHYL CELLULOSE, UNSPECIFIED; PHENOXYETHANOL; AMMONIUM ACRYLOYLDIMETHYLTAURATE, DIMETHYLACRYLAMIDE, LAURYL METHACRYLATE AND LAURETH-4 METHACRYLATE COPOLYMER, TRIMETHYLOLPROPANE TRIACRYLATE CROSSLINKED (45000 MPA.S); SODIUM CITRATE, UNSPECIFIED FORM; PHYTATE SODIUM

BLAIR & JACK Anti-Bump Acne Treatment Cream

Active ingredient

Benzoyl peroxide 5.00%

Purpose

Acne Treatment

Uses

- For the treatment of acne and shaving bumps

Warnings

For external use only.

When using this product

- Use a sunscreen
- Avoid contact with the eyes, lips and mouth
- Avoid contact with hair and dyed fabrics (may be bleached by this product).

Keep out of reach of children.

If swallowed, get medical help or contact a Poison Control Center right away

If pregnant or breast-feeding,

ask a health professional before use.

Do not use if you

- have very sensitive skin
- are sensitive to benzoyl peroxide.

Directions

- After cleansing the skin, apply the medication to the affected areas in the morning.

Other information

Protect the product in this container from excessive heat and direct sun.

Inactive ingredients

Allantoin, Aloe Barbadensis Leaf (Aloe Vera Gel) Juice, Aminomethyl Propanol, Aqua (Deionized Water), Behenyl Alcohol, Calendula Officinalis Extract, Camellia Sinensis (Green Tea) Extract, Caprylic/Capric Triglyceride, Carbomer, Cymbopogon Schoenanthus (Lemongrass) Oil, Dimethicone, Dioscorea Villosa (Wild Yam) Extract, Ethylhexylglycerin, Glycerin, Hamamelis Virginiana (Witch Hazel), Hydroxyethylcellulose, Phenoxyethanol, Polyacrylate Crosspolymer-6, Sodium Citrate, Sodium Phytate.

Question?

1-844-970-1256